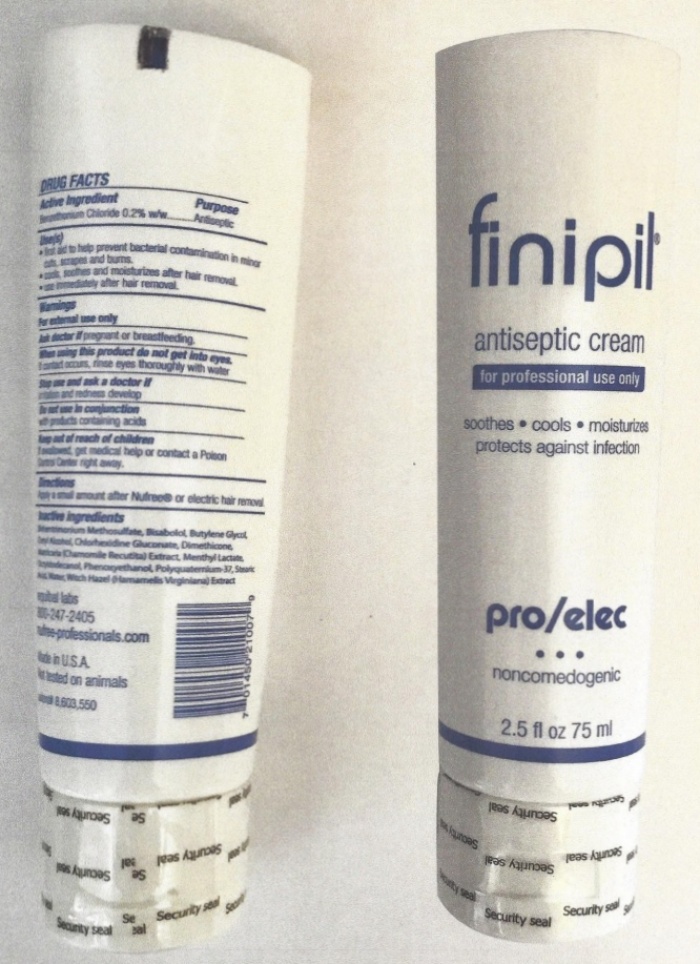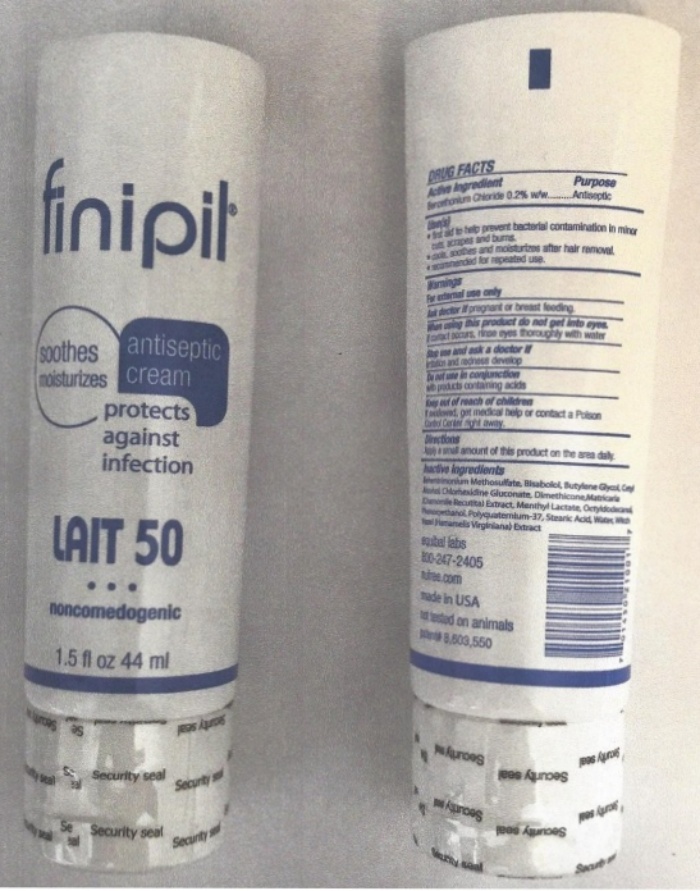 DRUG LABEL: finipil Lait 50
NDC: 53228-050 | Form: CREAM
Manufacturer: Equibal, Inc.
Category: otc | Type: HUMAN OTC DRUG LABEL
Date: 20251216

ACTIVE INGREDIENTS: BENZETHONIUM CHLORIDE 195 mg/100 mL
INACTIVE INGREDIENTS: BEHENTRIMONIUM METHOSULFATE; LEVOMENOL; BUTYLENE GLYCOL; CETYL ALCOHOL; CHLORHEXIDINE GLUCONATE; DIMETHICONE; MATRICARIA RECUTITA; MENTHYL LACTATE, (-)-; OCTYLDODECANOL; PHENOXYETHANOL; POLYQUATERNIUM-37 (25000 MPA.S); STEARIC ACID; WATER; HAMAMELIS VIRGINIANA TOP

finipil Lait 50

Active Ingredient

DRUG FACTS
Active Ingredient
Benzethonium Chloride 0.2% w/w

Purpose

Antiseptic

Keep out of reach of children.

If swallowed, get medical help or contact a Poison Control Center right away.

Use(s)

- first aid to help prevent bacterial contamination in minor cuts, scrapes and burns.
- cools, soothes and moisturizes after hair removal.
- recommended for repeated use.

Warnings Do not use in conjunction

Warnings

For external use only

Do not use in conjunction

with products containing acids

Ask a doctor if

Ask a doctor ifpregnant or breast feeding,

Stop use and ask a doctor if

irritation and redness develop

Directions

Apply a small amount of this product on the area daily.

When using this product do not get into eyes.
If contact occurs, rinse eyes thoroughly with water.

Inactive ingredients

Behentrimonium methosulfate, Bisabolol, Butylene Glycol, Cetyl Alcohol, Chlorhexidine Gluconate, Dimethicone, Matricaria (Chamomile Recutita) Extract, Menthyl Lactate, Octyldodecanol, Phenoxyethanol, Polyquarternium-37, Stearic Acid, Witch Hazel (Hamamelis Virginiana) Extract

finipil LAIT 50 Product Label

finipil®

soothes antiseptic

moisturizes cream

protects

against

infection

LAIT 50

●●●

Noncomedogenic

1.5 fl oz 44 ml

DRUG FACTS

Active Ingredient Purpose

Benzethonium Chloride 0.2% w/w Antiseptic

Uses(s)

- first aid to help prevent bacterial contamination in minor cuts, scrapes, and burns.
- cools, soothes, and moisturizes after hair removal.
- recommended for repeated use.

Warnings

For external use only

Ask a doctor ifpregnant or breast feeding.

When using this product do not get into eyes.

if contact occurs, rinse eyes thoroughly with water

Stop use and ask a doctor if

irritation and redness develop

Do not use in conjunction

with products containing acids.

Keep out of reach of children

if swallowed, get medical help or contact a Poison Control Center right away.

Directions

Apply a small amount of this product on the area daily.

Inactive Ingredients

Behentrimonium Methosulfate, Bisabolol, Butylene Glycol, Cetyl Alcohol, Chlorhexidine Gluconate, Dimethicone, Matricaria (Chamomile Recutital) Extract, Menthyl Lactate, Octylodecanoil, Phenoxyethanol, Polyquaterniuim-37, Stearic Acid, Water, Witch Hazel (Hamamelis Virginiana) Extract

equibal labs

800-247-2405

nufree.com

Made in U.S.A.

not tested on animals

patent# 8,603,550